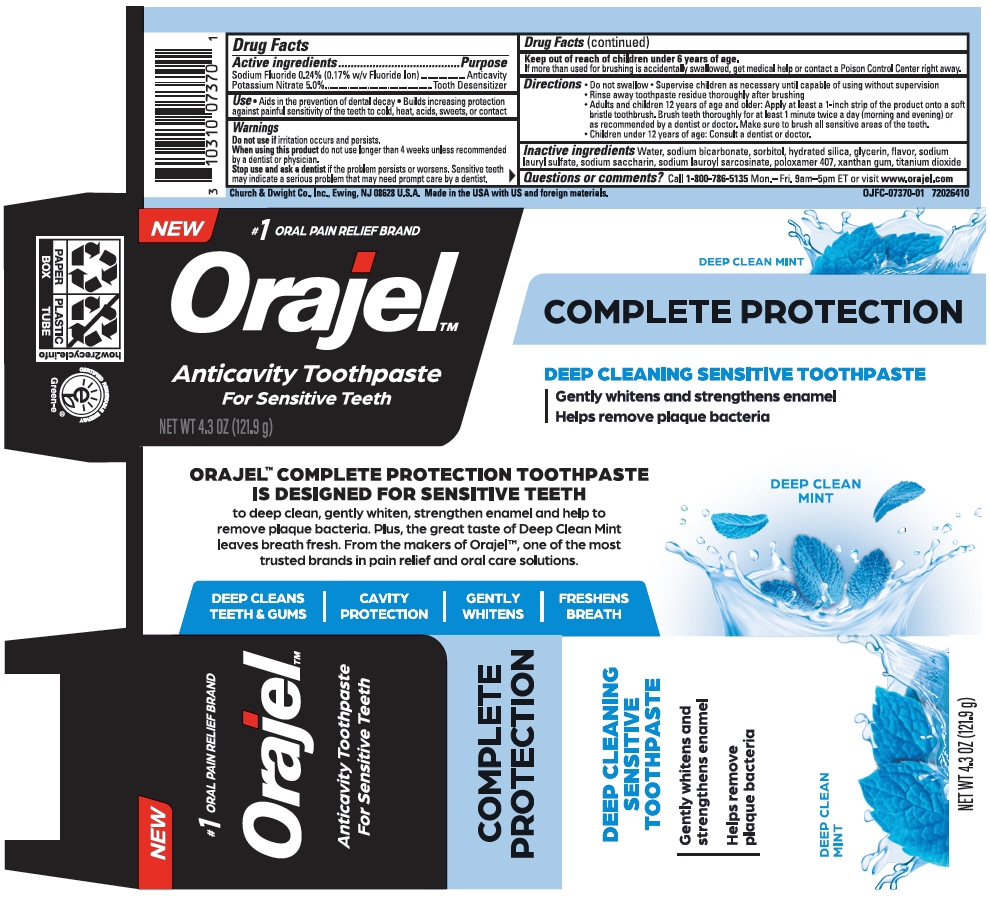 DRUG LABEL: Orajel Complete Protection
NDC: 10237-677 | Form: PASTE
Manufacturer: Church & Dwight Co., Inc.
Category: otc | Type: HUMAN OTC DRUG LABEL
Date: 20231219

ACTIVE INGREDIENTS: SODIUM FLUORIDE 0.243 g/100 g; POTASSIUM NITRATE 5 g/100 g
INACTIVE INGREDIENTS: WATER; SODIUM BICARBONATE; SORBITOL; HYDRATED SILICA; GLYCERIN; SODIUM LAURYL SULFATE; SODIUM LAUROYL SARCOSINATE; POLOXAMER 407; XANTHAN GUM; TITANIUM DIOXIDE

Orajel™ Complete Protection Toothpaste

Drug Facts

ACTIVE INGREDIENT

Active ingredients | Purpose
Sodium Fluoride 0.24% (0.17% w/v Fluoride Ion) | Anticavity
Potassium Nitrate 5.0% | Tooth Desensitizer

Use

- Aids in the prevention of dental decay
- Builds increasing protection against painful sensitivity of the teeth to cold, heat, acids, sweets, or contact

Warnings

Do not use if irritation occurs and persists.

When using this product do not use longer than 4 weeks unless recommended by a dentist or physician.

Stop use and ask a dentist if the problem persists or worsens. Sensitive teeth may indicate a serious problem that may need prompt care by a dentist.

Keep out of reach of children under 6 years of age.

If more than used for brushing is accidentally swallowed, get medical help or contact a Poison Control Center right away.

Directions

- Do not swallow
- Supervise children as necessary until capable of using without supervision
- Rinse away toothpaste residue thoroughly after brushing
- Adults and children 12 years of age and older: Apply at least a 1-inch strip of the product onto a soft bristle toothbrush. Brush teeth thoroughly for at least 1 minute twice a day (morning and evening) or as recommended by a dentist or doctor. Make sure to brush all sensitive areas of the teeth.
- Children under 12 years of age: Consult a dentist or doctor.

Inactive ingredients

Water, sodium bicarbonate, sorbitol, hydrated silica, glycerin, flavor, sodium lauryl sulfate, sodium saccharin, sodium lauroyl sarcosinate, poloxamer 407, xanthan gum, titanium dioxide

Questions or comments?

Call 1-800-786-5135 Mon.– Fri. 9am–5pm ET or visit www.orajel.com

PRINCIPAL DISPLAY PANEL - 121.9 g Tube Carton

NEW

#1 ORAL PAIN RELIEF BRAND

Orajel™

Anticavity Toothpaste
For Sensitive Teeth

DEEP CLEAN MINT

COMPLETE PROTECTION

DEEP CLEANING SENSITIVE TOOTHPASTE

Gently whitens and strengthens enamel
Helps remove plaque bacteria

NET WT 4.3 OZ (121.9 g)